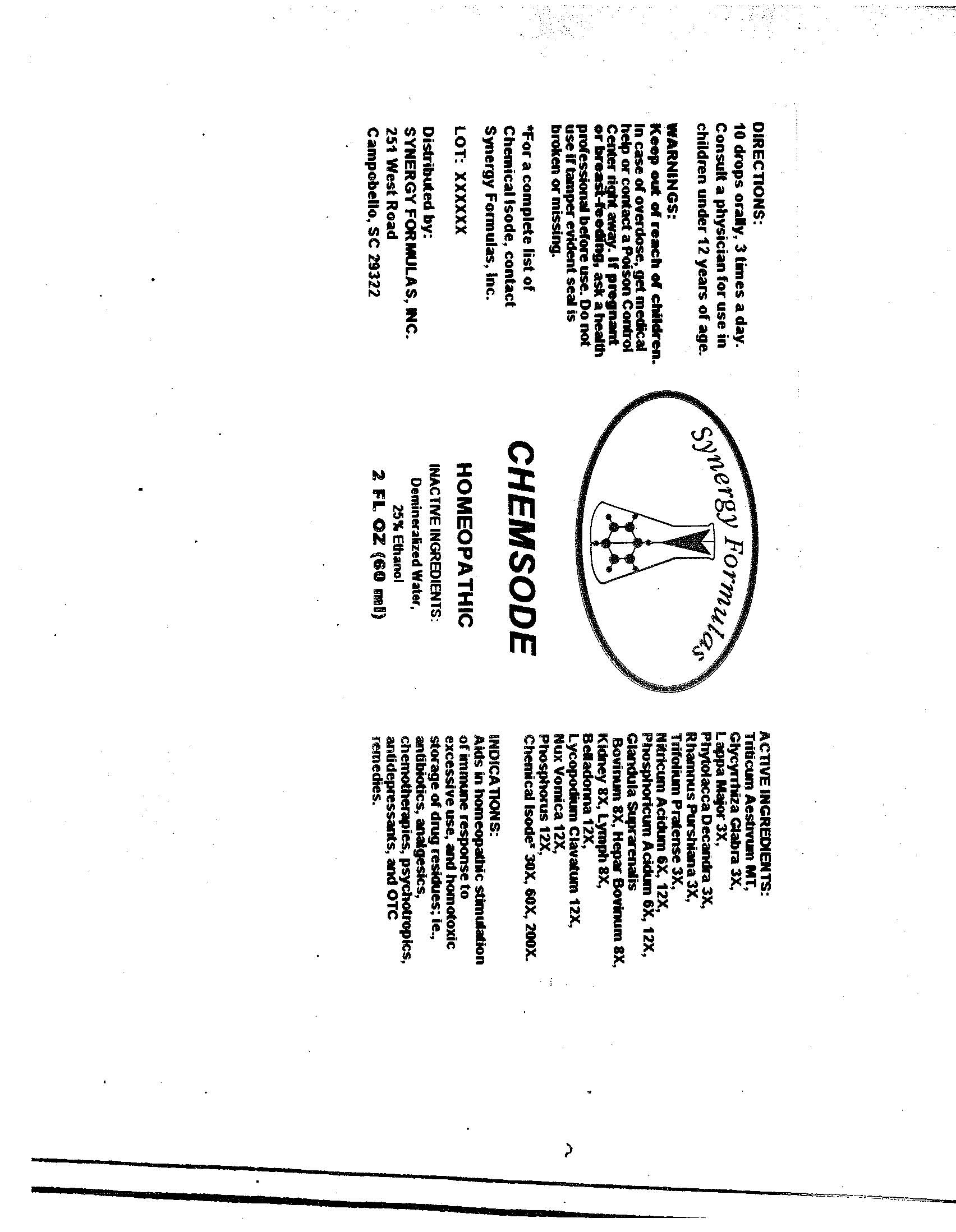 DRUG LABEL: Chemsode
NDC: 57520-0554 | Form: LIQUID
Manufacturer: Apotheca Company
Category: homeopathic | Type: HUMAN OTC DRUG LABEL
Date: 20100716

ACTIVE INGREDIENTS: WHEAT 1 [hp_X]/1 mL; GLYCYRRHIZA GLABRA 3 [hp_X]/1 mL; ARCTIUM LAPPA ROOT 3 [hp_X]/1 mL; PHYTOLACCA AMERICANA ROOT 3 [hp_X]/1 mL; FRANGULA PURSHIANA BARK 3 [hp_X]/1 mL; RED CLOVER 3 [hp_X]/1 mL; NITRIC ACID 12 [hp_X]/1 mL; PHOSPHORIC ACID 12 [hp_X]/1 mL; BOS TAURUS ADRENAL GLAND 8 [hp_X]/1 mL; BEEF LIVER 8 [hp_X]/1 mL; PORK KIDNEY 8 [hp_X]/1 mL; SUS SCROFA LYMPH 8 [hp_X]/1 mL; ATROPA BELLADONNA 12 [hp_X]/1 mL; LYCOPODIUM CLAVATUM SPORE 12 [hp_X]/1 mL; STRYCHNOS NUX-VOMICA SEED 12 [hp_X]/1 mL; PHOSPHORUS 12 [hp_X]/1 mL; SALICYLIC ACID 200 [hp_X]/1 mL; CORTICOTROPIN 200 [hp_X]/1 mL; CORTISONE ACETATE 200 [hp_X]/1 mL; EUGENOL 200 [hp_X]/1 mL; STEARYL ALCOHOL 200 [hp_X]/1 mL; XYLITOL 200 [hp_X]/1 mL; ESTRONE 200 [hp_X]/1 mL; BENZOIC ACID 200 [hp_X]/1 mL; CHLORINE 200 [hp_X]/1 mL; POTASSIUM SORBATE 200 [hp_X]/1 mL; SORBITOL 200 [hp_X]/1 mL; RESORCINOL 200 [hp_X]/1 mL; BENZYL ALCOHOL 200 [hp_X]/1 mL; LACTIC ACID, DL- 200 [hp_X]/1 mL; ISOPROPYL PALMITATE 200 [hp_X]/1 mL; BORIC ACID 200 [hp_X]/1 mL; ACETIC ACID 200 [hp_X]/1 mL; PHENYLBUTAZONE 200 [hp_X]/1 mL; PETROLATUM 200 [hp_X]/1 mL; LEAD 200 [hp_X]/1 mL
INACTIVE INGREDIENTS: WATER; ALCOHOL

Chemsode

ACTIVE INGREDIENT

ACTIVE INGREDIENTS: Triticum aestivum 1X, Glycyrrhiza glabra 3X, Lappa major 3X, Phytolacca decandra 3X, Rhamnus purshiana 3X, Trifolium pratense 3X, Nitricum acidum 6X, 12X, Phosphoricum acidum 6X, 12X, Glandula suprarenalis bovinum 8X, Hepar bovinum 8X, Kidney 8X, Lymph 8X, Belladonna 12X, Lycopodium clavatum 12X, Nux vomica 12X, Phosphorus 12X, Salicylicum acidum 30X, 60X, 200X, Adrenocorticotrophin 30X, 60X, 200X, Cortisone aceticum 30X, 60X, 200X, Eugenol 30X, 60X, 200X, Stearyl alcohol 30X, 60X, 200X, Xylitol 30X, 60X, 200X, Folliculinum 30X, 60X, 200X, Benzoicum acidum 30X, 60X, 200X, Chlorinum 30X, 60X, 200X, Potassium sorbate 30X, 60X, 200X, Sorbitol 30X, 60X, 200X, Resorcinol 30X, 60X, 200X, Benzyl alcohol 30X, 60X, 200X, Lacticum acidum 30X, 60X, 200X, Isopropyl palmitate 30X, 60X, 200X, Boricum acidum 30X, 60X, 200X, Aceticum acidum 30X, 60X, 200X, Phenylbutazone 30X, 60X, 200X, Petroleum jelly 30X, 60X, 200X, Plumbum metallicum 30X, 60X, 200X.

PURPOSE

INDICATIONS: Aids in homeopathic stimulation of immune response to excessive use, and homotoxic storage of drug residues; ie., antibiotics, analgesics, chemotherapies, psychotropics, antidepressants, and OTC remedies.

WARNINGS

WARNINGS: Keep out of reach of children. In case of overdose, get medical help or contact a Poison Control Center right away.

If pregnant or breast-feeding, ask a health professional before use.

Do not use if tamper evident seal is broken or missing.

DOSAGE AND ADMINISTRATION

DIRECTIONS: 10 drops orally, 3 times a day. Consult a physician for use in children under 12 years of age.

INACTIVE INGREDIENTS: Demineralized water, 25% Ethanol.

QUESTIONS

Distributed by:

SYNERGY FORMULAS, INC.

251 West Road

Campobello, SC 29322

PACKAGE LABEL

Synergy Formulas

CHEMSODE

HOMEOPATHIC

2 FL OZ (60 ml)